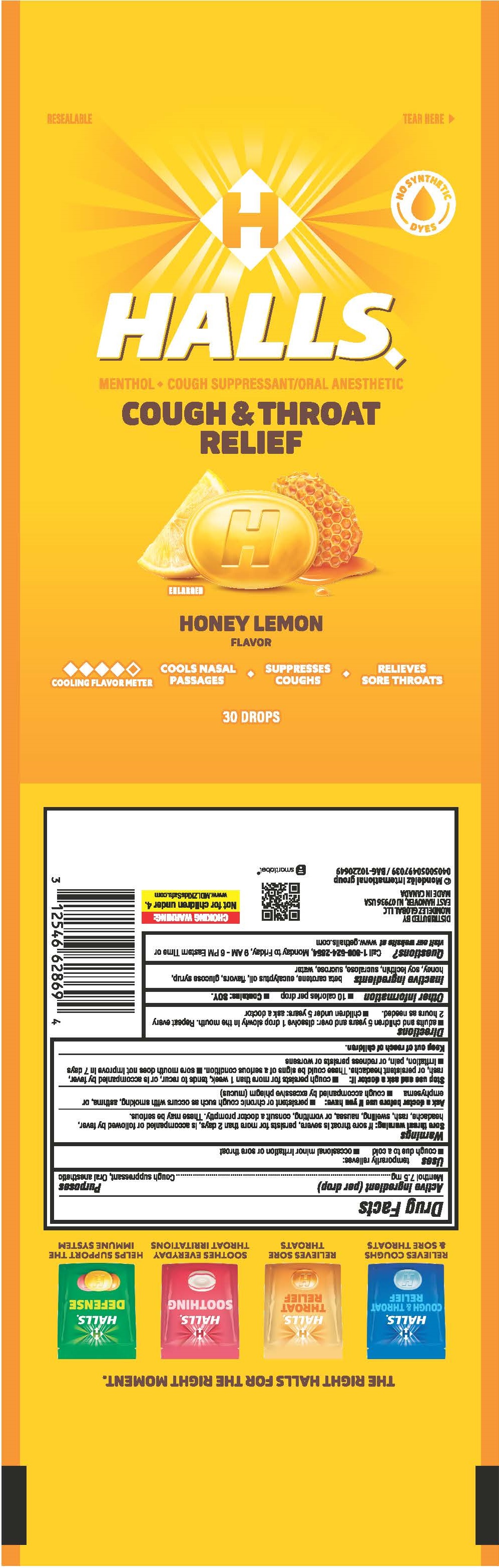 DRUG LABEL: Halls
NDC: 12546-110 | Form: LOZENGE
Manufacturer: Mondelez Global LLC
Category: otc | Type: HUMAN OTC DRUG LABEL
Date: 20250616

ACTIVE INGREDIENTS: MENTHOL 7.5 mg/1 1
INACTIVE INGREDIENTS: HONEY; LECITHIN, SOYBEAN; SUCRALOSE; SUCROSE; WATER; EUCALYPTUS OIL; .BETA.-CAROTENE

HALLS HONEY LEMON bag

Active ingredient

<(per drop) Menthol 7.5 mg>

Purposes

<Cough suppressant, Oral Anesthetic>

Uses

<temporarily relieves:>

- cough due to a cold
- occasional minor irritation or sore throat

Warnings

<Sore throat warning: if sore throat is severe, persists for more than 2 days, is accompanied or followed by fever, headache, rash, swelling, nausea, or vomiting, consult a doctor promptly. These may be serious.>

Ask a doctor before use if you have

- persistent or chronic cough such as occurs with smoking, asthma, or emphysema
- cough accompanied by excessive phlegm (mucus)

Stop use and ask a doctor if

- cough persists for more than 1 week, tends to recur, or is accompanied by fever, rash, or persistent headache. These could be signs of a serious condition.
- sore mouth does not improve in 7 days
- irritation, pain, or redness persists or worsens

Keep out of reach of children

Enter section text here

Directions

- adults and children 5 years and over: dissolve 1 drop slowly in the mouth. Repeat every 2 hours as needed.
- children under 5 years: ask a doctor

Other information

- 10 calories per drop
- Contains: SOY.

Inactive ingredients

<beta carotene, eucalyptus oil, flavors, glucose syrup, honey, soy lecithin, sucralose, sucrose, water>

Questions

<Call 1-800-524-2854, Monday to Friday, 9 AM-6PM Eastern Time or visit our website at www.gethalls.com>